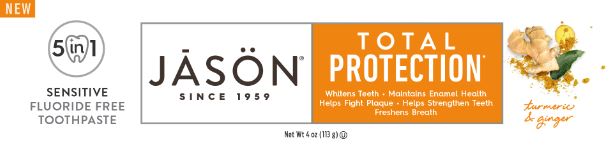 DRUG LABEL: Jason Total Protection Sensitive
NDC: 61995-1562 | Form: PASTE, DENTIFRICE
Manufacturer: The Hain Celestial Group, Inc
Category: otc | Type: HUMAN OTC DRUG LABEL
Date: 20210412

ACTIVE INGREDIENTS: POTASSIUM NITRATE 5 g/100 g
INACTIVE INGREDIENTS: CALCIUM CARBONATE; HYDRATED SILICA; PEPPERMINT OIL; CARBOXYMETHYLCELLULOSE; GLYCERIN; WATER; SODIUM BICARBONATE; CURCUMA LONGA WHOLE; XYLITOL; SODIUM COCOYL GLUTAMATE; SODIUM SULFATE; ETLINGERA ELATIOR WHOLE; CLOVE OIL

Jason Total Protection Sensitive Toothpaste

ACTIVE INGREDIENT

Potassium Nitrate 5%

PURPOSE

Tooth desensitizer

WARNINGS

Sensitive teeth may indicate a seriuos problem that may need prompt care by a dentist. See your dentist if the problem persists or warsens. Do not use this product longer than 4 weeks unless recommended by a dentist or doctor.

KEEP OUT OF REACH OF CHILDREN

Keep out of the reach of children under 6 years of age. If you accidentally swallow more than used for brushing, seek professional assistance immediately.

INDICATIONS AND USAGE

Tooth desensitizer

INACTIVE INGREDIENT

Calcium Carbonate, Glycerin, Water (Aqua), Xylitol, Hydrated Silica, Sodium Cocoyl Glutamate, Flavor, Eugenia Caryophyllus (Clove) Flower Oil, Mentha Piperita (Peppermint) Oil, Curcuma Longa (Turmeric) Root Extract (1), Etlingera Elatior Flower Extract, Cellulose Gum, Sodium Bicarbonate, Sodium Magnesium Silicate, Sodium Sulfate.

(1) Certified Organic Ingredient

DOSAGE AND ADMINISTRATION

Potassium Nitrate 5%.

Directions: Adults and children 12 years of age and older: Apply at least a 1-inch strip of the product onto a soft bristled toothbrush. Brush teeth thoroughly for at least 1 minute twice a day (morning and evening) or as recommended by a dentist or doctor. Make sure to brush all sensitive areas of the teeth. Children under 12 years of age: Consult a dentist or doctor.